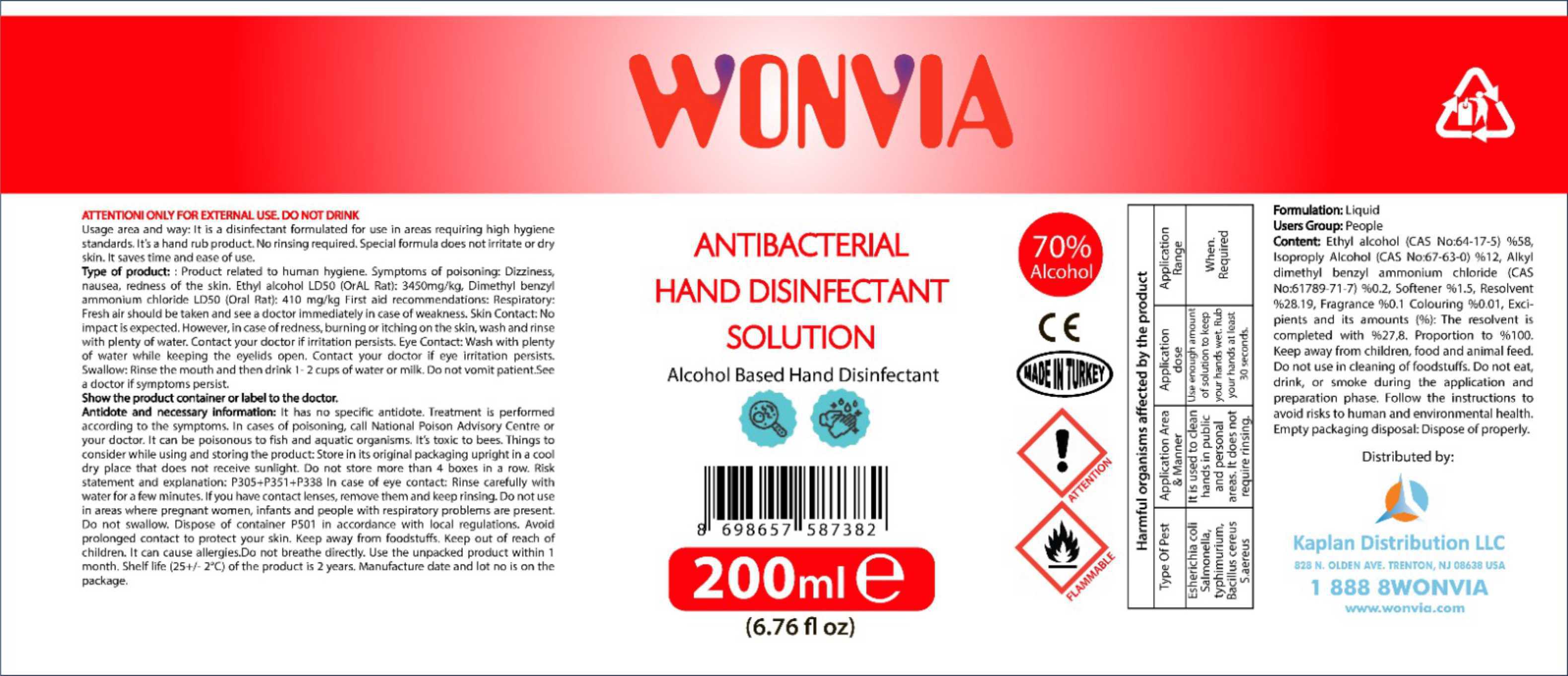 DRUG LABEL: Wonvia Antibacterial Hand Disinfectant Sanitizer
NDC: 78876-712 | Form: SOLUTION
Manufacturer: KAPLAN DISTRIBUTION LLC
Category: otc | Type: HUMAN OTC DRUG LABEL
Date: 20200806

ACTIVE INGREDIENTS: ISOPROPYL ALCOHOL 12 g/100 mL; BENZALKONIUM CHLORIDE 0.2 g/100 mL; ALCOHOL 58 g/100 mL
INACTIVE INGREDIENTS: WATER

Active Ingredient(s)

Alcohol 70% Purpose: Antibacterial Hand Disinfectant

Purpose

Antibacterial Hand Disinfectant Solution

Use

Hand Sanitizer to help reduce bacteria that potentially can cause disease. For use when soap and water are not available.

Warnings

For external use only. Flammable. Keep away from heat or flame

Do not use

- Keep away from children
- on open skin wounds
- do not use in the cleaning of foodstuffs

When using this product keep out of eyes, ears, and mouth. In case of contact with eyes, rinse eyes thoroughly with plenty of water.
Stop use and ask a doctor if irritation or rash occurs. These may be signs of a serious condition.
Keep out of reach of children. If swallowed, get medical help or contact a Poison Control Center right away. Do not breathe directly.

Stop use and ask a doctor if irritation or rash occurs. These may be signs of a serious condition.

Keep out of reach of children. If swallowed, get medical help or contact a Poison Control Center right away.

Directions

- Use enough amount of product to keep your hands wet. Rub hands together for 30 seconds.
- Keep away from children, food, and animal feed.
- Follow the instructions to avoid risks to human and environmental health.

Other information

- Store between 15-30C (59-86F) in its original packaging upright in a cool dry place that does not receive sunlight.
- Avoid freezing and excessive heat above 40C (104F)
- Do not store more than 4 boxes in a row.
- Dispose of the container P501 in accordance with local regulations.
- Use the unpacked product within 1 month.
- Shelf life (25+/-2C) of the product is 2 years.

Inactive ingredients

Softener 1.5%, resolvent 28.19%, fragrance 0.1%, colouring 0.01%

resolvent is completed with 27.8% proportion to 100%

Package Label - Principal Display Panel

200 mL NDC: 78876-712-02